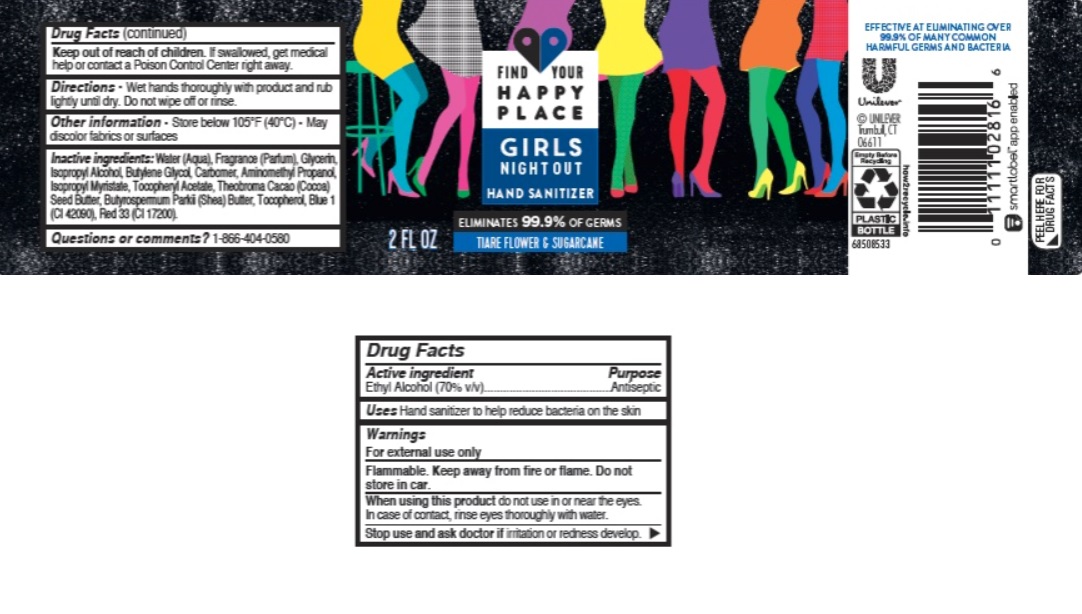 DRUG LABEL: Find Your Happy Place
NDC: 64942-1828 | Form: GEL
Manufacturer: Conopco Inc. d/b/a/ Unilever
Category: otc | Type: HUMAN OTC DRUG LABEL
Date: 20241107

ACTIVE INGREDIENTS: ALCOHOL 700 mg/1 mL
INACTIVE INGREDIENTS: COCOA BUTTER; .ALPHA.-TOCOPHEROL ACETATE; SHEA BUTTER; TOCOPHEROL; FD&C BLUE NO. 1; AMINOMETHYLPROPANOL; WATER; GLYCERIN; BUTYLENE GLYCOL; CARBOMER HOMOPOLYMER, UNSPECIFIED TYPE; ISOPROPYL ALCOHOL; ISOPROPYL MYRISTATE; D&C RED NO. 33

Find Your Happy Place Girls Night Out Hand Sanitizer

FIND YOUR HAPPY PLACE GIRLS NIGHT OUT HAND SANITIZER - Ethyl Alcohol gel

Find Your Happy Place Girls Night Out Hand Sanitizer

Drug Facts

Active ingredient

Ethyl Alcohol 70 %

Purpose

Antiseptic

Uses

Hand sanitizer to help reduce bacteria on the skin

Warnings

For external use only
Flammable. Keep away from fire or flame. Do not store in car .
When using this product do not use in or near the eyes.
Stop use and ask doctor if irritation or redness develop.

• Keep out of reach of children except under adult supervision.

If swallowed, get medical help or contact a Poison Control Center right away.

Directions

Wet hands thoroughly with product and rub lightly until dry. Do not wipe off or rinse.

Other information

Store below 105˚F (40˚C). May discolor fabrics or surfaces.

Inactive ingredients

Water (Aqua), Fragrance (Parfum), Glycerin, Isopropyl Alcohol, Butylene Glycol, Carbomer, Aminomethyl Propanol, Isopropyl Myristate, Tocopheryl Acetate, Theobroma Cacao (Cocoa) Seed Butter, Butyrospermum Parkii (Shea) Butter, Tocopherol, Blue 1 (CI 42090), Red 33 (CI 17200).

Questions or comments?

1-800-404-0580